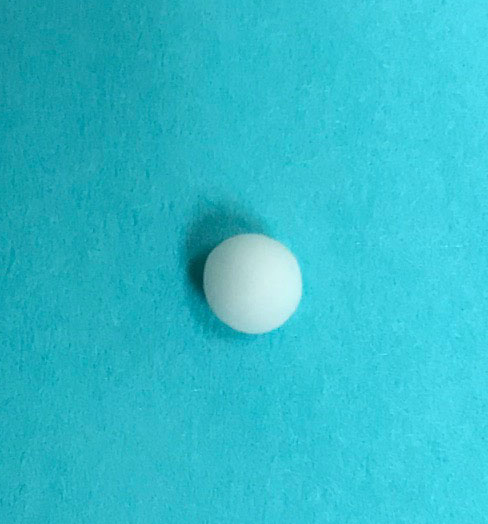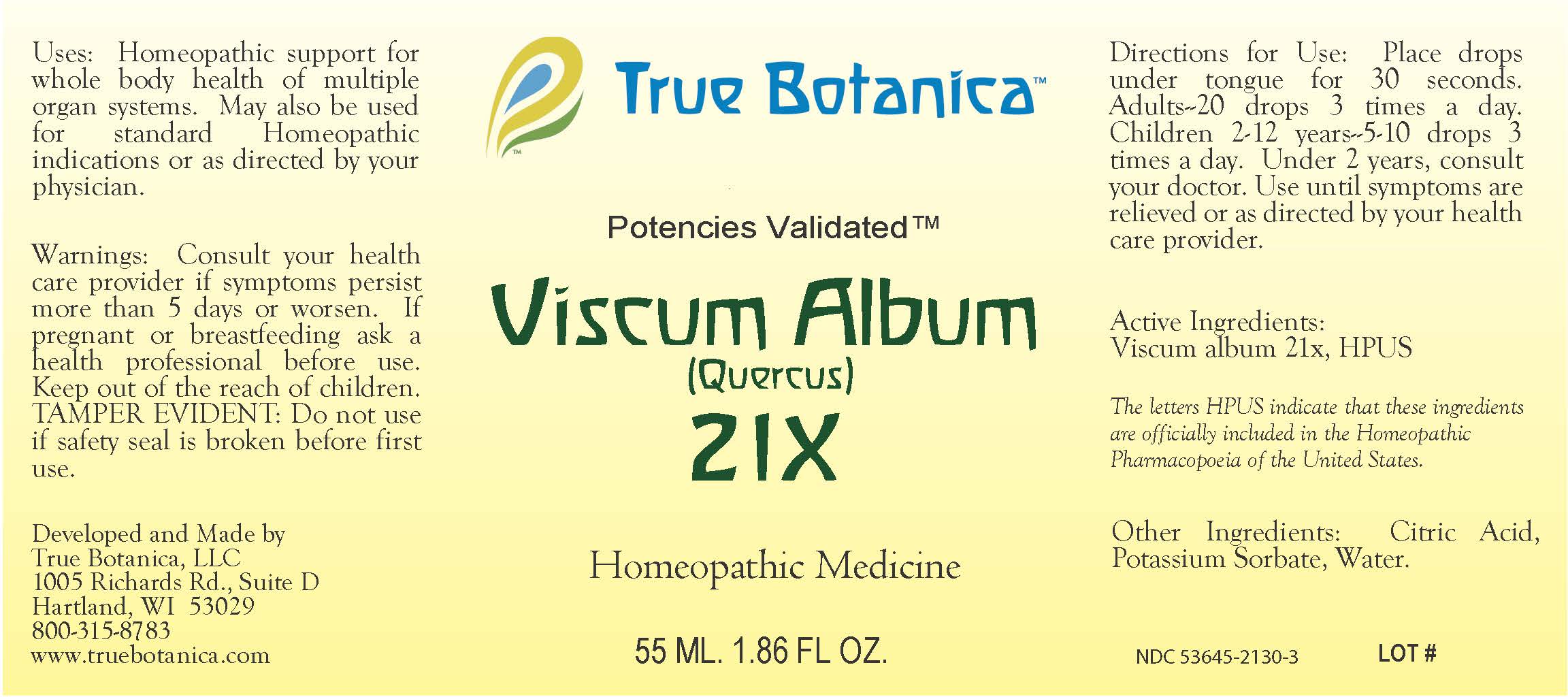 DRUG LABEL: Pulsatilla
NDC: 53645-2130 | Form: GLOBULE
Manufacturer: True Botanica, LLC
Category: homeopathic | Type: HUMAN OTC DRUG LABEL
Date: 20191221

ACTIVE INGREDIENTS: VISCUM ALBUM LEAF 21 [hp_X]/23 g
INACTIVE INGREDIENTS: SUCROSE

Viscum Album 21X

ACTIVE INGREDIENT

Viscum Album 21X, HPUS

The letters HPUS indicate that these ingredients are officially included in the Homeopathic Pharmacopoeia of the United States.

PURPOSE

Homeopathic support for whole body health of multiple organ systems.May also be used for standard homeopathic indications or as directed by your physician.

Use:

Homeopathic support for whole body health of multiple organ systems.May also be used for standard homeopathic indications or as directed by your physician.

Warnings:

Consult your health care provider if symptoms persist more than 5 days or worsen.

PREGNANCY OR BREAST FEEDING

If pregnant or breastfeeding ask a health professional before use.

Keep out of the reach of children.

DO NOT USE

TAMPER EVIDENT: Do not use if safety seal is broken before first use.

Directions for Use:

Place drops under tongue for 30 seconds. Adults 20 drops 3 times a day. Children 2-12years 5-10 drops 3 times a day. Under 2 years, consult your doctor. Use until symptoms are relieved or as directed by your health care provider.

Other Ingredients:

Citric Acid, Potassium Sorbate, Water.

QUESTIONS

Developed and Made by

True Botanica, LLC

1005 Richards Rd., Suite D

Hartland, WI 53029

800-315-8783

www.truebotanica.com